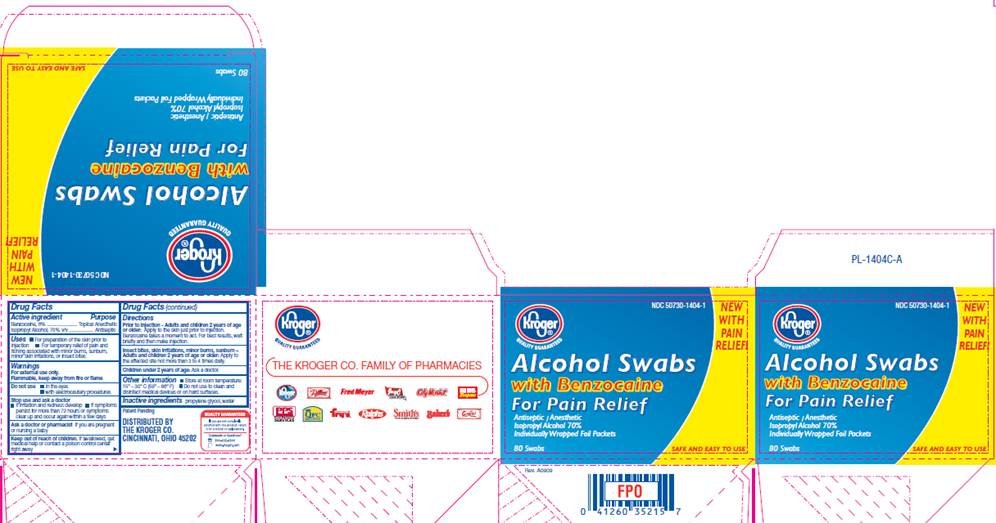 DRUG LABEL: Alcohol Swabs with Benzocaine
NDC: 50730-1404 | Form: SWAB
Manufacturer: Triad Group
Category: otc | Type: HUMAN OTC DRUG LABEL
Date: 20100416

ACTIVE INGREDIENTS: benzocaine 0.06 mL/1 1; isopropyl alcohol 0.70 mL/1 1
INACTIVE INGREDIENTS: propylene glycol; water

DRUG FACTS

ACTIVE INGREDIENTS

Benzocaine 6%
Isopropyl alcohol 70% v/v

PURPOSE

Topical Anesthetic

Antiseptic

USES

- For preparation of the skin prior to injection
- For temporary relief of pain and itching associated with minor burns, sunburn, minor skin irritations, or insect bites

WARNINGS

For external use only.
Flammable, keep away from fire or flame.

Do not use

- in the eyes
- with electrocautery procedures

Stop use and ask a doctor

- if irritation and redness develop
- if symptoms persist for more than 72 hours or symptoms clear up and occur within a few days.

Ask a doctor or pharmacist

if you are pregnant or nursing a baby.

Keep out of reach of children

If swallowed, get medical help or contact a Poison Control Center right away.

DIRECTIONS

Prior to Injection - Adults and children 2 years of age or older:
Apply to the skin just prior to injection. Benzocaine takes a minute to act. for best results, wait briefly and then make injection.
Insect bites, skin irritations, minor burns, sunburn -
Adults and children 2 years of age or older:
Apply to the affected site not more than 3 to 4 times daily.
Children under 2 years of age: Ask a doctor.

OTHER INFORMATION

- Store at room temperature: 15° - 30° C (59° - 86° F)
- Do not use to clean and disinfect medical devices or on hard surfaces

INACTIVE INGREDIENTS

propylene glycol, water

CARTON INFORMATION

Kroger®
Quality Guaranteed

NDC 50730-1404-1

NEW WITH PAIN RELIEF

Alcohol Swabs
with Benzocaine
For Pain Relief

Antiseptic / Anesthetic
Isopropyl alcohol 70%
Individually Wrapped Foil Packets

80 Swabs

SAFE AND EASY TO USE

DISTRIBUTED BY
THE KROGER CO.
CINCINNATI, OHIO 45202
QUALITY GUARANTEED
If you are not completely
satisfied with this product, return
it for a refund or replacement.
Comments or Questions?
800-632-6900
www.kroger.com